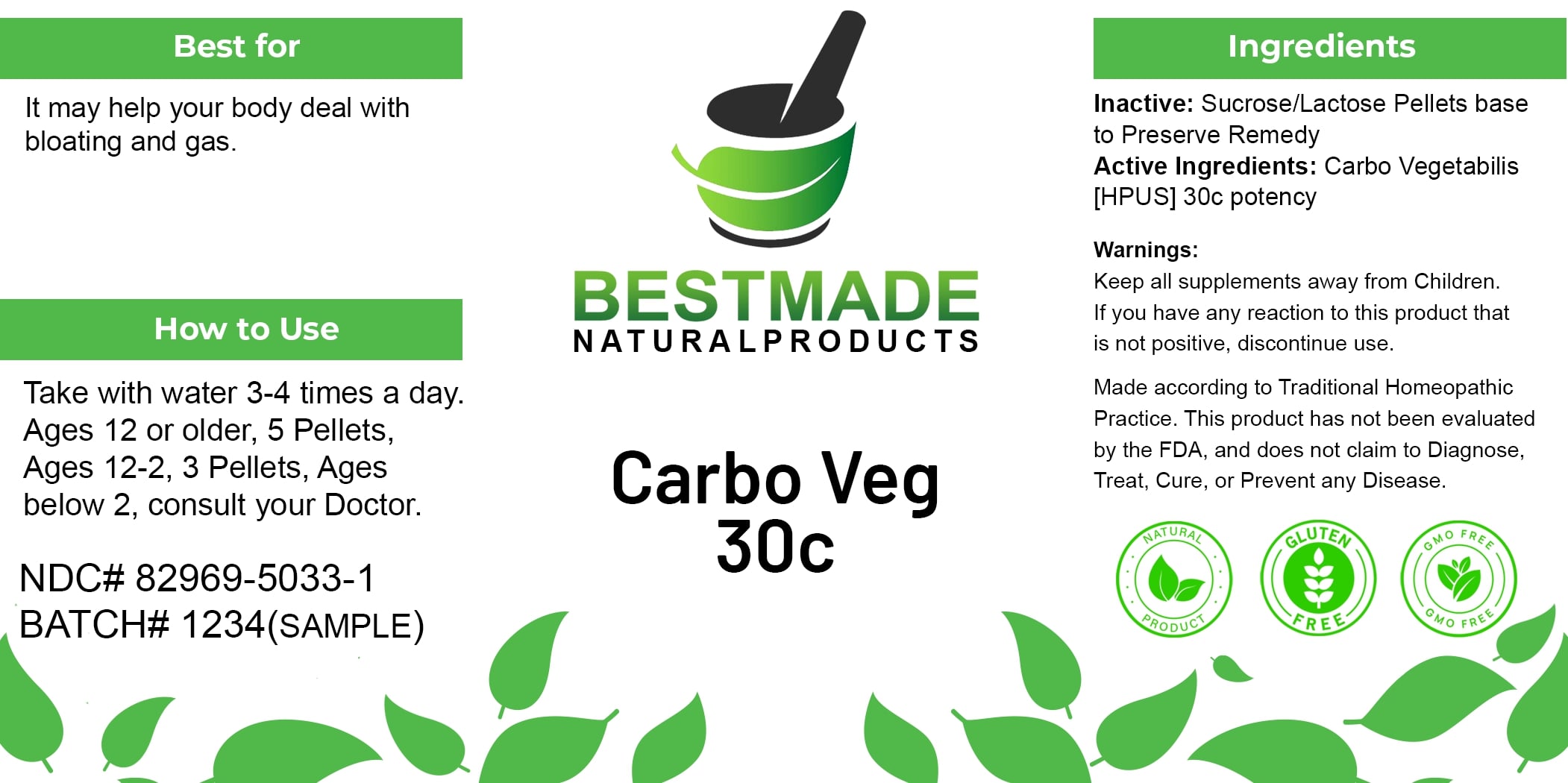 DRUG LABEL: Bestmade Natural Products Carbo Vegetabilis
NDC: 82969-5033 | Form: TABLET, SOLUBLE
Manufacturer: Bestmade Natural Products
Category: homeopathic | Type: HUMAN OTC DRUG LABEL
Date: 20241219

ACTIVE INGREDIENTS: ACTIVATED CHARCOAL 30 [hp_C]/30 [hp_C]
INACTIVE INGREDIENTS: SUCROSE 30 [hp_C]/30 [hp_C]; LACTOSE 30 [hp_C]/30 [hp_C]

CARBO VEGETABILIS 30C

DOSAGE AND ADMINISTRATION

How to Use

Take with water 3-4 times a day.

Ages 12 or older, 5 Pellets, Ages 12-2, 3 Pellets, Ages below 2, consult your Doctor.

INDICATIONS AND USAGE

Best for

It may help your body deal with bloating and gas.

PURPOSE

Best for

It may help your body deal with bloating and gas.

INACTIVE INGREDIENT

Ingredients

Inactive: Sucrose/Lactose Pellets base to Preserve Remedy

Active Ingredients: Carbo Vegetabilis [HPUS] 30c potency

Warnings:

Keep all supplements away from Children.

If you have any reaction to this product that is not positive, discontinue use.

Made according to Traditional Homeopathic Practice. This product has not been evaluated by the FDA, and does not claim to Diagnose, Treat, Cure, or Prevent any Disease.

Warnings:

Keep all supplements away from Children.

If you have any reaction to this product that is not positive, discontinue use.

Made according to Traditional Homeopathic Practice. This product has not been evaluated by the FDA, and does not claim to Diagnose, Treat, Cure, or Prevent any Disease.

Entire package label